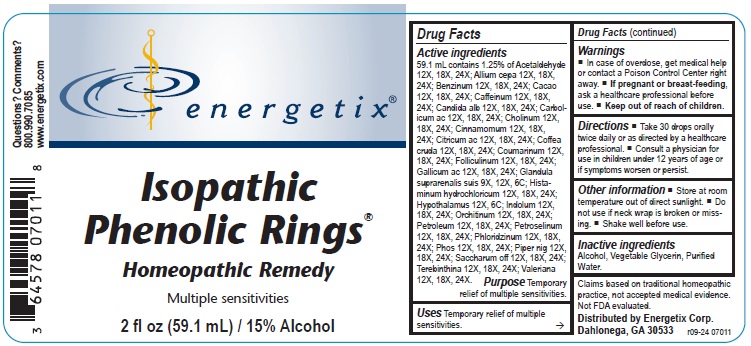 DRUG LABEL: Isopathic Phenolic Rings
NDC: 64578-0109 | Form: LIQUID
Manufacturer: Energetix Corporation
Category: homeopathic | Type: HUMAN OTC DRUG LABEL
Date: 20241120

ACTIVE INGREDIENTS: ACETALDEHYDE 12 [hp_X]/59.1 mL; ONION 12 [hp_X]/59.1 mL; BENZENE 12 [hp_X]/59.1 mL; COCOA 12 [hp_X]/59.1 mL; CAFFEINE 12 [hp_X]/59.1 mL; CANDIDA ALBICANS 12 [hp_X]/59.1 mL; PHENOL 12 [hp_X]/59.1 mL; CHOLINE 12 [hp_X]/59.1 mL; CINNAMON 12 [hp_X]/59.1 mL; ANHYDROUS CITRIC ACID 12 [hp_X]/59.1 mL; ARABICA COFFEE BEAN 12 [hp_X]/59.1 mL; COUMARIN 12 [hp_X]/59.1 mL; ESTRONE 12 [hp_X]/59.1 mL; GALLIC ACID 12 [hp_X]/59.1 mL; SUS SCROFA ADRENAL GLAND 9 [hp_X]/59.1 mL; HISTAMINE 12 [hp_X]/59.1 mL; BOS TAURUS HYPOTHALAMUS 12 [hp_X]/59.1 mL; INDOLE 12 [hp_X]/59.1 mL; BOS TAURUS TESTICLE 12 [hp_X]/59.1 mL; KEROSENE 12 [hp_X]/59.1 mL; PETROSELINUM CRISPUM 12 [hp_X]/59.1 mL; PHLORIZIN 12 [hp_X]/59.1 mL; PHOSPHORUS 12 [hp_X]/59.1 mL; GREEN PEPPERCORN 12 [hp_X]/59.1 mL; SUCROSE 12 [hp_X]/59.1 mL; TURPENTINE OIL 12 [hp_X]/59.1 mL; VALERIAN 12 [hp_X]/59.1 mL
INACTIVE INGREDIENTS: WATER; GLYCERIN; ALCOHOL

Isopathic Phenolic Rings

ACTIVE INGREDIENT

Active ingredients 59.1 mL contains 1.25% of:

Acetaldehyde 12X, 18X, 24X; Allium cepa 12X, 18X, 24X; Benzinum 12X, 18X, 24X; Cacao 12X, 18X, 24X; Caffeinum 12X, 18X, 24X; Candida alb 12X, 18X, 24X; Carbolicum ac 12X, 18X, 24X; Cholinum 12X, 18X, 24X; Cinnamomum 12X, 18X, 24X; Citricum ac 12X, 18X, 24X; Coffea cruda 12X, 18X, 24X; Coumarinum 12X, 18X, 24X; Folliculinum 12X, 18X, 24X; Gallicum ac 12X, 18X, 24X; Glandula suprarenalis suis 9X, 12X, 6C; Histaminum hydrochloricum 12X, 18X, 24X; Hypothalamus 12X, 6C; Indolum 12X, 18X, 24X; Orchitinum 12X, 18X, 24X; Petroleum 12X, 18X, 24X; Petroselinum sativum 12X, 18X, 24X; Phloridzinum 12X, 18X, 24X; Phos 12X, 18X, 24X; Piper nig 12X, 18X, 24X; Saccharum off 12X, 18X, 24X; Terebinthina 12X, 18X, 24X; Valeriana 12X, 18X, 24X.

Claims based on traditional homeopathic practice, not accepted medical evidence. Not FDA evaluated.

Uses

Temporary relief of multiple sensitivities.

Warnings

- In case of overdose, get medical help or contact a Poison Control Center right away.
- If pregnant or breast-feeding, ask a healthcare professional before use.

- Keep out of reach of children.

Directions

- Take 30 drops orally twice daily or as directed by a healthcare professional.
- Consult a physician for use in children under 12 years of age or if symptoms worsen or persist.

Other information

- Store at room temperature out of direct sunlight.
- Do not use if neck wrap is broken or missing.
- Shake well before use.

Inactive ingredients

Alcohol, Vegetable Glycerin, Purified Water.

QUESTIONS

Distributed by Energetix Corp.

Dahlonega, GA 30533

Questions? Comments?

800.990.7085

www.energetix.com

PACKAGE LABEL

energetix

Isopathic Phenolic Rings

Homeopathic Remedy

Multiple sensitivities

2 fl oz (59.1 mL) / 15% Alcohol

Purpose Temporary relief of multiple sensitivities.